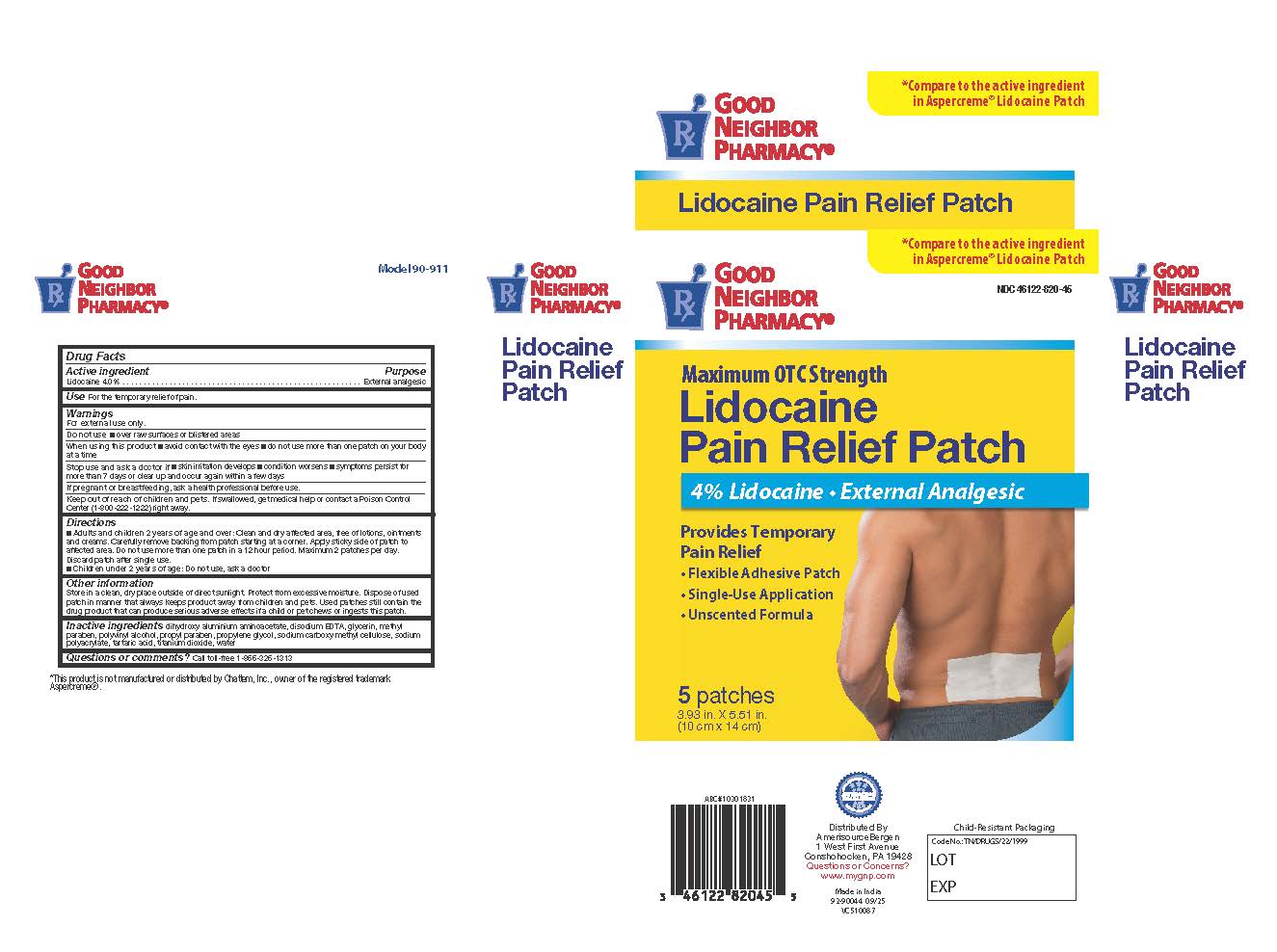 DRUG LABEL: Good Neighbor Pain Relief Patch With Lidocaine 4%
NDC: 46122-820 | Form: PATCH
Manufacturer: Amerisource Bergen
Category: otc | Type: HUMAN OTC DRUG LABEL
Date: 20250918

ACTIVE INGREDIENTS: LIDOCAINE 4 g/100 g
INACTIVE INGREDIENTS: GLYCERIN; METHYLPARABEN; PROPYLENE GLYCOL; PROPYLPARABEN; SODIUM POLYACRYLATE (2500000 MW); TARTARIC ACID; TITANIUM DIOXIDE; WATER; DIHYDROXYALUMINUM AMINOACETATE; POLYVINYL ALCOHOL; EDETATE DISODIUM; CARBOXYMETHYLCELLULOSE SODIUM

Good Neighbor Pain Relief Patch With Lidocaine 4%

Active Ingredients

Lidocaine 4% . . . . . . . . . . . . . . . . . . . . . . . . . . . . . . External analgesic

Purpose

External analgesic

Dosage and Administration

Directions
■ Adults and children 2 years of age and over: Clean and dry affected area, free of lotions, ointments and creams. Carefully remove backing from patch starting at a corner. Apply sticky side of patch to affected area. Do not use more than one patch in a i 2 hour period. Maximum 2 patches per day. Discard patch after single use.
■ Children under 2 years of age: Do not use, ask a doctor

Warnings

For external use only.

Indications and Usage

Uses: Temporaily relieves minor pains.

When using this product■avoid contact with the eyes ■ do not use more than one patch on your body at a time.

Stop use and consult a doctor

Stop use and ask a doctor if

■ skin irritation develops ■ condition worsens ■symptoms persist for more than 7 days or clear up and occur again within a few days

PREGNANCY OR BREAST FEEDING

If pregnant or breastfeeding, ask a health professional before use.

Do not Use

- Over raw surfaces or blistered areas

Keep out of reach of children and pets.

If swallowed, get medical help or contact a Poison Control Center (1-800-222-1222) right away.

Other Safety Information

Other information

Store in a clean, dry place outside of direct sunlight. Protect from excessive moisture. Dispose of used patch in manner that always keeps product away from children and pets. Used patches still contain the drug product that can produce serious adverse effects if a child or pet chews or
ingests this patch.

Inactive Ingredients

Inactive ingredients: dihydroxy aluminium aminoacetate, disodium EDTA, glycerin, methylparaben, polyvinyl alcohol, propyl paraben, propylene glycol, sodium carboxy methyl cellulose, sodiumpolyacrylate, tartaric acid, titanium dioxide, water

Questions

CALL TOLL-FREE 1-866-326-1313